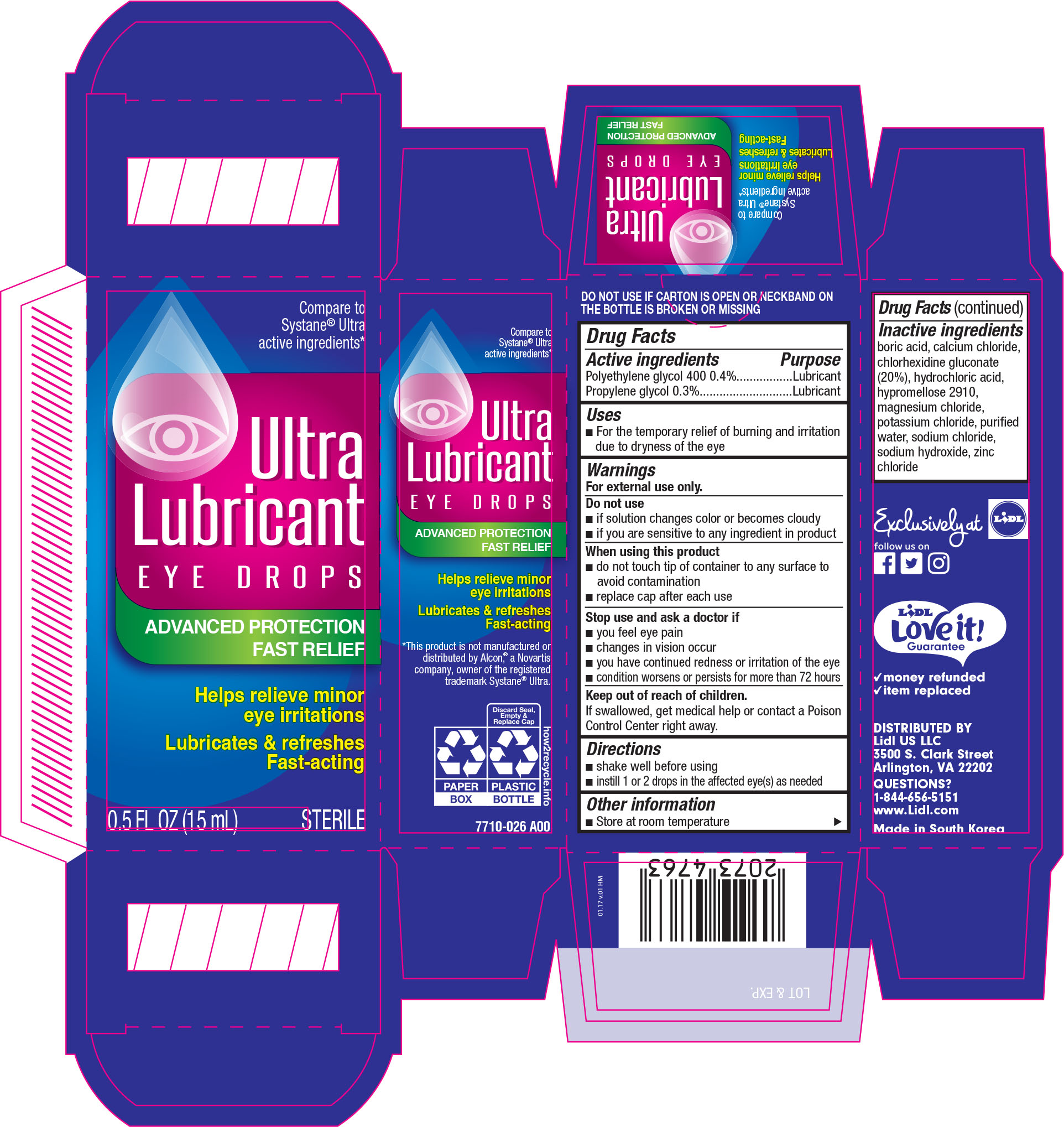 DRUG LABEL: Lidl Ultra Lubricant Eye
NDC: 71141-150 | Form: SOLUTION/ DROPS
Manufacturer: Lidl US, LLC
Category: otc | Type: HUMAN OTC DRUG LABEL
Date: 20170310

ACTIVE INGREDIENTS: POLYETHYLENE GLYCOL 400 4 mg/1 mL; PROPYLENE GLYCOL 3 mg/1 mL
INACTIVE INGREDIENTS: BORIC ACID; CALCIUM CHLORIDE; CHLORHEXIDINE GLUCONATE; HYDROCHLORIC ACID; HYPROMELLOSE 2910 (15 MPA.S); MAGNESIUM CHLORIDE; POTASSIUM CHLORIDE; WATER; SODIUM CHLORIDE; SODIUM HYDROXIDE; ZINC CHLORIDE

Active ingredients Purpose

Polyethylene glycol 400 0.4%..............................Lubricant

Propylene glycol 0.3%........................................Lubricant

Uses

- For the temporary relief of burning and irritation due to dryness of the eye

Warnings

For external use only.

Do not use

- if solution changes color or becomes cloudy
- if you are sensitive to any ingredient in product

When using this product

- do not touch tip of container to any surface to avoid contamination
- replace cap after each use

Stop use and ask a doctor if

- you feel eye pain
- changes in vision occur
- you have continued redness or irritation of the eye
- condition worsens or persists for more than 72 hours

Keep out of reach of children.

If swallowed, get medical help or contact a Poison Control Center right away.

Directions

- shake well befure using
- instil 1 or 2 drops in the affected eye(s) as needed

Other information

- store at room temperature

Inactive ingredients

boric acid, calcium chloride, chlorhexidine gluconate (20%), hydrochloric acid, hypromellose 2910, magnesium chloride, potassium chloride,

purified water, sodium chloride, sodium hydroxide, zinc chloride

DOSAGE AND ADMINISTRATION

Distributed by:

Lidl US LCC

3500 S. Clark Street

Arlighton, VA 22202

Made in South Korea